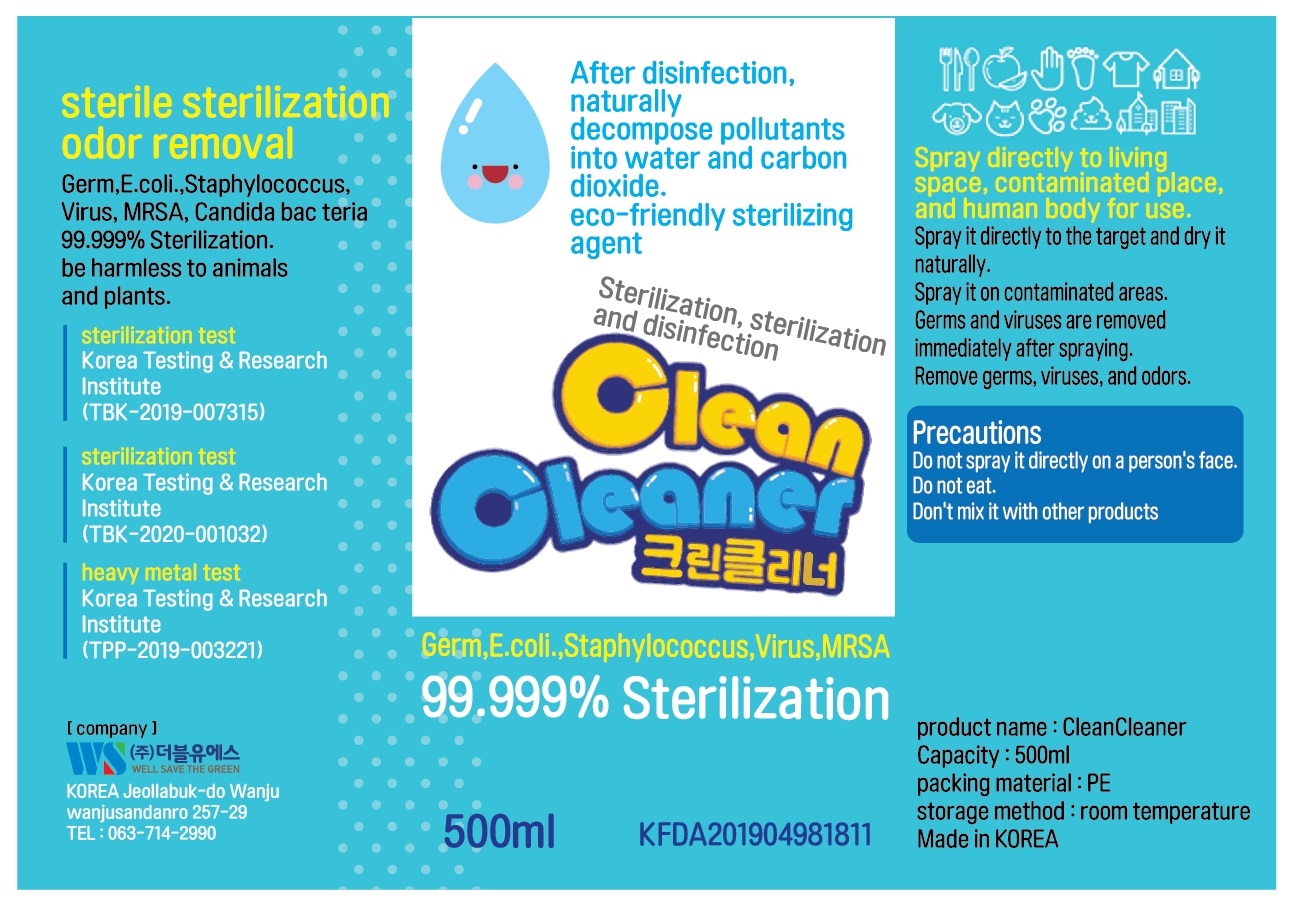 DRUG LABEL: CleanCleaner
NDC: 75534-0001 | Form: LIQUID
Manufacturer: WS
Category: otc | Type: HUMAN OTC DRUG LABEL
Date: 20200418

ACTIVE INGREDIENTS: HYDROGEN PEROXIDE 0.085 mL/70 mL
INACTIVE INGREDIENTS: GLYCERIN; ACETIC ACID; WATER

Drug Facts

ACTIVE INGREDIENT

hydrogen peroxide

INACTIVE INGREDIENT

acetic acid
Purified Water
an organic acid

PURPOSE

sterilization and disinfection

KEEP OUT OF REACH OF THE CHILDREN

INDICATIONS AND USAGE

Spray it directly to the target and dry it naturally.
Spray it on contaminated areas.
Germs and viruses are removed immediately after spraying.
Remove germs, viruses, and odors.
Do not spray it directly on a person's face.
Do not eat.

WARNINGS

For external use only.

Flammable, keep away from fire or flame.

When using this product keep out of eyes. If contact with eyes occurs, rinse promptly and thoroughly with water.

Stop use and ask a doctor if significant irritation or sensitization develops.

Keep out of reach of children. If swallowed, get medical help or contact a Poison Control Center right away.

DOSAGE AND ADMINISTRATION

for external use only